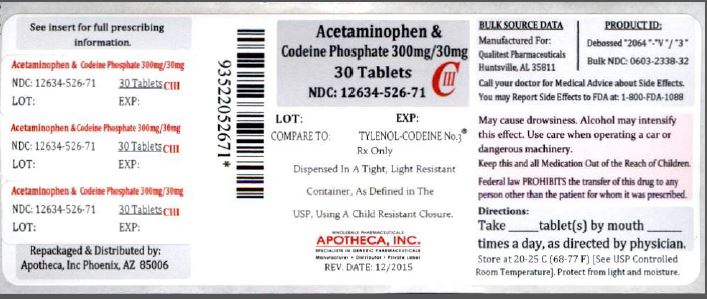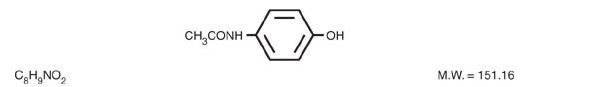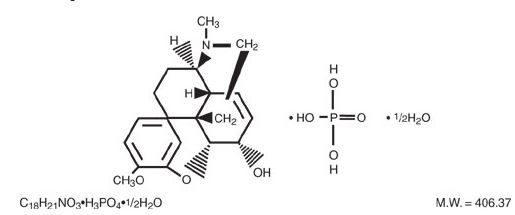 DRUG LABEL: ACETAMINOPHEN AND CODEINE PHOSPHATE
NDC: 12634-526 | Form: TABLET
Manufacturer: Apotheca, Inc.
Category: prescription | Type: HUMAN PRESCRIPTION DRUG LABEL
Date: 20160119
DEA Schedule: CIII

ACTIVE INGREDIENTS: ACETAMINOPHEN 300 mg/1 1; CODEINE PHOSPHATE 30 mg/1 1
INACTIVE INGREDIENTS: SILICON DIOXIDE; LACTOSE MONOHYDRATE; MAGNESIUM STEARATE; CELLULOSE, MICROCRYSTALLINE; SODIUM STARCH GLYCOLATE TYPE A POTATO

ACETAMINOPHEN AND CODEINE PHOSPHATE TABLETS USP CIII Rx Only

DESCRIPTION

Acetaminophen and codeine is supplied in tablet form for oral administration.

Acetaminophen, 4'‑hydroxyacetanilide, a slightly bitter, white, odorless, crystalline powder, is a non-opiate, non-salicylate analgesic and antipyretic. It has the following structural formula:

Codeine phosphate, 7,8‑didehydro‑4,5α‑epoxy‑3‑methoxy‑17‑methylmorphinan‑6α‑ol phosphate (1:1) (salt) hemihydrate, a white crystalline powder, is a narcotic analgesic and antitussive. It has the following structural formula:

Each tablet contains:

Acetaminophen...........................300 mg

Codeine Phosphate.......................15 mg

(Warning: May be habit forming)

OR

Acetaminophen...........................300 mg

Codeine Phosphate....................... 30 mg

(Warning: May be habit forming)

OR

Acetaminophen...........................300 mg

Codeine Phosphate....................... 60 mg

(Warning: May be habit forming)

In addition, each tablet contains the following inactive ingredients: Corn Starch, Colloidal Silicon Dioxide, Croscarmellose Sodium, Magnesium Stearate, and Microcrystalline Cellulose. The 300 mg/60 mg strength tablets also contain Crospovidone, Povidone, Pregelatinized Starch, and Stearic Acid. (Teva Pharmaceuticals).

In addition each tablet contains the following inactive ingredients: magnesium stearate, microcrystalline cellulose, povidone, pregelatinized corn starch, sodium metabisulfite, sodium starch glycolate and stearic acid. (Vintage Pharmaceuticals)

CLINICAL PHARMACOLOGY

This product combines the analgesic effects of a centrally acting analgesic, codeine, with a peripherally acting analgesic, acetaminophen.

Pharmacokinetics

The behavior of the individual components is described below.

Codeine

Codeine is readily absorbed from the gastrointestinal tract. It is rapidly distributed from the intravascular spaces to the various body tissues, with preferential uptake by parenchymatous organs such as the liver, spleen and kidney. Codeine crosses the blood-brain barrier, and is found in fetal tissue and breast milk. The plasma concentration does not correlate with brain concentration or relief of pain; however, codeine is not bound to plasma proteins and does not accumulate in body tissues.

The plasma half-life is about 2.9 hours. The elimination of codeine is primarily via the kidneys, and about 90% of an oral dose is excreted by the kidneys within 24 hours of dosing. The urinary secretion products consist of free and glucuronide conjugated codeine (about 70%), free and conjugated norcodeine (about 10%), free and conjugated morphine (about 10%), normorphine (4%), and hydrocodone (1%). The remainder of the dose is excreted in the feces.

At therapeutic doses, the analgesic effect reaches a peak within 2 hours and persists between 4 and 6 hours.

See OVERDOSAGE for toxicity information.

Acetaminophen

Acetaminophen is rapidly absorbed from the gastrointestinal tract and is distributed throughout most body tissues. The plasma half-life is 1.25 to 3 hours, but may be increased by liver damage and following overdosage. Elimination of acetaminophen is principally by liver metabolism (conjugation) and subsequent renal excretion of metabolites. Approximately 85% of an oral dose appears in the urine within 24 hours of administration, most as the glucuronide conjugate, with small amounts of other conjugates and unchanged drug.

See OVERDOSAGE for toxicity information.

INDICATIONS AND USAGE

Acetaminophen and codeine phosphate tablets are indicated for the relief of mild to moderately severe pain.

CONTRAINDICATIONS

This product should not be administered to patients who have previously exhibited hypersensitivity to codeine or acetaminophen.

WARNINGS

In the presence of head injury or other intracranial lesions, the respiratory depressant effects of codeine and other narcotics may be markedly enhanced, as well as their capacity for elevating cerebrospinal fluid pressure. Narcotics also produce other CNS depressant effects, such as drowsiness, that may further obscure the clinical course of the patients with head injuries.

Codeine or other narcotics may obscure signs on which to judge the diagnosis or clinical course of patients with acute abdominal conditions.

Codeine is habit-forming and potentially abusable. Consequently, the extended use of this product is not recommended.

Alcohol Information

Chronic heavy alcohol abusers may be at increased risk of liver toxicity from excessive acetaminophen use, although reports of this event are rare. Reports almost invariably involve cases of severe chronic alcoholics and the dosages of acetaminophen most often exceed recommended doses and often involve substantial overdose. Professionals should alert their patients who regularly consume large amounts of alcohol not to exceed recommended doses of acetaminophen

PRECAUTIONS

General

Acetaminophen and codeine phosphate tablets should be prescribed with caution in certain special-risk patients, such as the elderly or debilitated, and those with severe impairment of renal or hepatic function, head injuries, elevated intracranial pressure, acute abdominal conditions, hypothyroidism, urethral stricture, Addison's disease, or prostatic hypertrophy.

Information for Patients

Codeine may impair mental and or physical abilities required for the performance of potentially hazardous tasks such as driving a car or operating machinery. Such tasks should be avoided while taking this product.

Alcohol and other CNS depressants may produce an additive CNS depression, when taken with this combination product, and should be avoided.

Codeine may be habit forming. Patients should take the drug only for as long as it is prescribed, in the amounts prescribed, and no more frequently than prescribed.

Laboratory Tests

In patients with severe hepatic or renal disease, effects of therapy should be monitored with serial liver and/or renal function tests.

Drug Interactions

This drug may enhance the effects of: other narcotic analgesics, alcohol, general anesthetics, tranquilizers such as chlordiazepoxide, sedative-hypnotics, or other CNS depressants, causing increased CNS depression

Drug and/or Laboratory Test Interactions

Codeine may increase serum amylase levels.

Acetaminophen may produce false-positive test results for urinary 5-hydroxyindoleacetic acid.

Carcinogenesis and Mutagenesis and Impairment of Fertility

No adequate studies have been conducted in animals to determine whether acetaminophen and codeine have a potential for carcinogenesis or mutagenesis. No adequate studies have been conducted in animals to determine whether acetaminophen has a potential for impairment of fertility.

Acetaminophen and codeine have been found to have no mutagenic potential using the Ames Salmonella-Microsomal Activation test, the Basc test on Drosophila germ cells, and the Micronucleus test on mouse bone marrow

Pregnancy

Teratogenic Effects
Pregnancy category C

Codeine

A study in rats and rabbits reported no teratogenic effect of codeine administered during the period of organogenesis in doses ranging from 5 to 120 mg/kg. In the rat, doses at the 120 mg/kg level, in the toxic range for the adult animal, were associated with an increase in embryo resorption at the time of implantation. In another study a single 100 mg/kg dose of codeine administered to pregnant mice reportedly resulted in delayed ossification in the offspring.

There are no adequate and well-controlled studies in pregnant women. Acetaminophen and codeine phosphate should be used during pregnancy only if the potential benefit justifies the potential risk to the fetus.

Nonteratogenic Effects

Dependence has been reported in newborns whose mothers took opiates regularly during pregnancy. Withdrawal signs include irritability, excessive crying, tremors, hyperreflexia, fever, vomiting, and diarrhea. These signs usually appear during the first few days of life.

Labor and Delivery

Narcotic analgesics cross the placental barrier. The closer to delivery and the larger the dose used, the greater the possibility of respiratory depression in the newborn. Narcotic analgesics should be avoided during labor if delivery of a premature infant is anticipated. If the mother has received narcotic analgesics during labor, newborn infants should be observed closely for signs of respiratory depression. Resuscitation may be required (see OVERDOSAGE). The effect of codeine, if any, on the later growth, development, and functional maturation of the child is unknown

Nursing Mothers

Acetaminophen and codeine are excreted in breast milk in small amounts, but the significance of their effects on nursing infants is not known. Because of the potential for serious adverse reactions in nursing infants from acetaminophen and codeine, a decision should be made whether to discontinue nursing or to discontinue the drug, taking into account the importance of the drug to the mother.

ADVERSE REACTIONS

The most frequently reported adverse reactions are drowsiness, lightheadedness, dizziness, sedation, shortness of breath, nausea and vomiting. These effects seem to be more prominent in ambulatory than in non-ambulatory patients, and some of these adverse reactions may be alleviated if the patient lies down.

Other adverse reactions include allergic reactions, euphoria, dysphoria, constipation, abdominal pain, pruritus, rash, thrombocytopenia, agranulocytosis.

At higher doses codeine has most of the disadvantages of morphine including respiratory depression.

DRUG ABUSE AND DEPENDENCE

Controlled Substance

Acetaminophen and codeine phosphate tablets are classified as a Schedule III controlled substance.

Abuse and Dependence

Codeine can produce drug dependence of the morphine type and, therefore, has the potential for being abused. Psychological dependence, physical dependence, and tolerance may develop upon repeated administration and it should be prescribed and administered with the same degree of caution appropriate to the use of other oral narcotic medications

OVERDOSAGE

Following an acute overdosage, toxicity may result from codeine or acetaminophen.

Signs and Symptoms

Codeine

Toxicity from codeine poisoning includes the opioid triad of: pinpoint pupils, depression of respiration, and loss of consciousness. Convulsions may occur.

Acetaminophen

In acetaminophen overdosage: dose-dependent, potentially fatal hepatic necrosis is the most serious adverse effect. Renal tubular necrosis, hypoglycemic coma and thrombocytopenia may also occur.

Early symptoms following a potentially hepatotoxic overdose may include: nausea, vomiting, diaphoresis and general malaise. Clinical and laboratory evidence of hepatic toxicity may not be apparent until 48 to 72 hours post-ingestion.

In adults, hepatic toxicity has rarely been reported with acute overdoses of less than 10 grams, or fatalities with less than 15 grams.

Treatment

A single or multiple overdose with acetaminophen and codeine is a potentially lethal polydrug overdose, and consultation with a regional poison control center is recommended.

Immediate treatment includes support of cardiorespiratory function and measures to reduce drug absorption. Vomiting should be induced mechanically, or with syrup of ipecac, if the patient is alert (adequate pharyngeal and laryngeal reflexes). Oral activated charcoal (1 g/kg) should follow gastric emptying. The first dose should be accompanied by an appropriate cathartic. If repeated doses are used, the cathartic might be included with alternate doses as required. Hypotension is usually hypovolemic and should respond to fluids. Vasopressors and other supportive measures should be employed as indicated. A cuffed endo-tracheal tube should be inserted before gastric lavage of the unconscious patient and, when necessary, to provide assisted respiration.

Meticulous attention should be given to maintaining adequate pulmonary ventilation. In severe cases of intoxication, peritoneal dialysis, or preferably hemodialysis may be considered. If hypoprothrombinemia occurs due to acetaminophen overdose, vitamin K should be administered intravenously.

Naloxone, a narcotic antagonist, can reverse respiratory depression and coma associated with opioid overdose. Naloxone hydrochloride 0.4 mg to 2 mg is given parenterally. Since the duration of action of codeine may exceed that of the naloxone, the patient should be kept under continuous surveillance and repeated doses of the antagonist should be administered as needed to maintain adequate respiration. A narcotic antagonist should not be administered in the absence of clinically significant respiratory or cardiovascular depression.

If the dose of acetaminophen may have exceeded 140 mg/kg, acetylcysteine should be administered as early as possible. Serum acetaminophen levels should be obtained, since levels four or more hours following ingestion help predict acetaminophen toxicity. Do not await acetaminophen assay results before initiating treatment. Hepatic enzymes should be obtained initially, and repeated at 24 hour intervals.

Methemoglobinemia over 30% should be treated with methylene blue by slow intravenous administration.

Toxic Doses (for adults)

Acetaminophen: toxic dose 10 g

Codeine: toxic dose 240 mg

DOSAGE AND ADMINISTRATION

Dosage should be adjusted according to severity of pain and response of the patient.

The usual adult dosage is:

 | Single Doses (range) | Maximum 24 Hour Dose
Codeine Phosphate | 15 mg to 60 mg | 360 mg
Acetaminophen | 300 mg to 1000 mg | 4000 mg

The usual dose of codeine phosphate in children is 0.5 mg/kg.

Doses may be repeated up to every 4 hours.

The prescriber must determine the number of tablets per dose, and the maximum number of tablets per 24 hours based upon the above dosage guidance. This information should be conveyed in the prescription.

It should be kept in mind, however, that tolerance to codeine can develop with continued use and that the incidence of untoward effects is dose related. Adult doses of codeine higher than 60 mg fail to give commensurate relief of pain but merely prolong analgesia and are associated with an appreciably increased incidence of undesirable side effects. Equivalently high doses in children would have similar effects.

HOW SUPPLIED

Acetaminophen and Codeine Phosphate Tablets 300 mg/30 mg are white, round, flat-faced, beveled edge, scored (bisect bar) tablets, debossed "2064" and "V" on one side and debossed "3" on the reverse side. They are supplied in bottles of 30, 50, 60, 90, 100, 120, 180, 500 and 1000.

Acetaminophen and Codeine Phosphate Tablets 300 mg/60 mg are white, round, flat-faced, beveled edge, scored (bisect bar) tablets, debossed "2065" and "V" on one side and debossed "4" on the reverse side. They are supplied in bottles of 100, 500 and 1000.

Storage and Dispensing

Dispense in a tight, light resistant container as defined in the USP/NF.

Store at 20° to 25°C (68° to 77°F) [see USP Controlled Room Temperature].